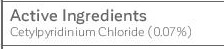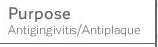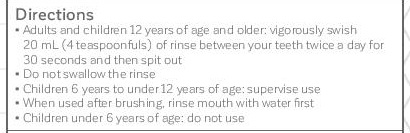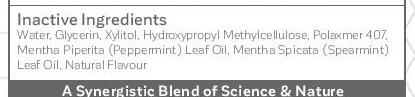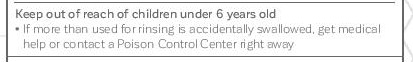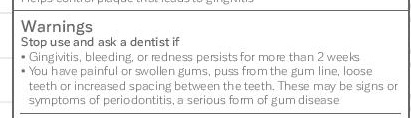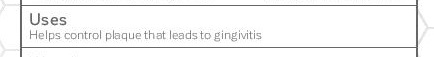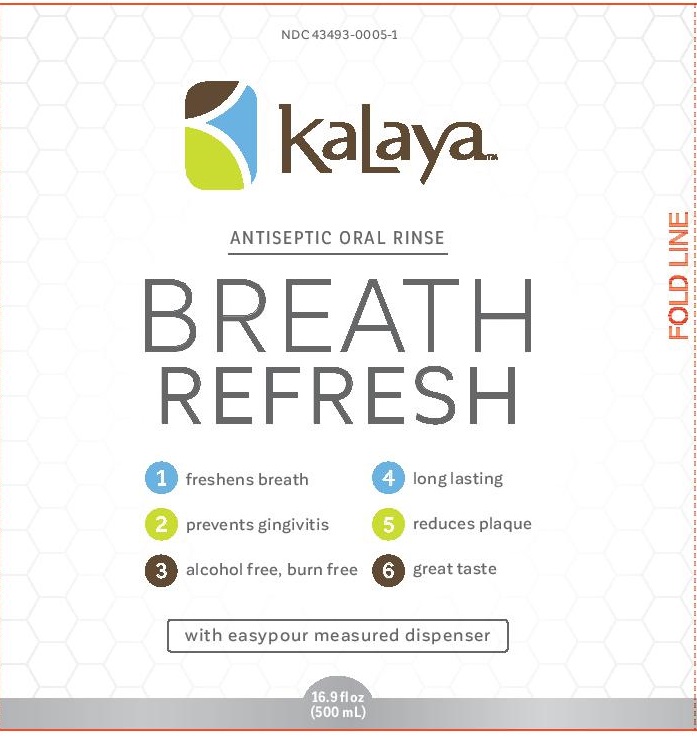 DRUG LABEL: Kalaya Breath Refresh
NDC: 43493-0005 | Form: LIQUID
Manufacturer: Avaria Health and Beauty Corp
Category: otc | Type: HUMAN OTC DRUG LABEL
Date: 20251008

ACTIVE INGREDIENTS: CETYLPYRIDINIUM CHLORIDE 0.7 mg/1 mL
INACTIVE INGREDIENTS: XYLITOL; GLYCERIN; HYPROMELLOSES; WATER; POLOXAMER 407; PEPPERMINT OIL; SPEARMINT OIL

Kalaya Breath Refresh Antiseptic Oral Rinse-updated label for NDC